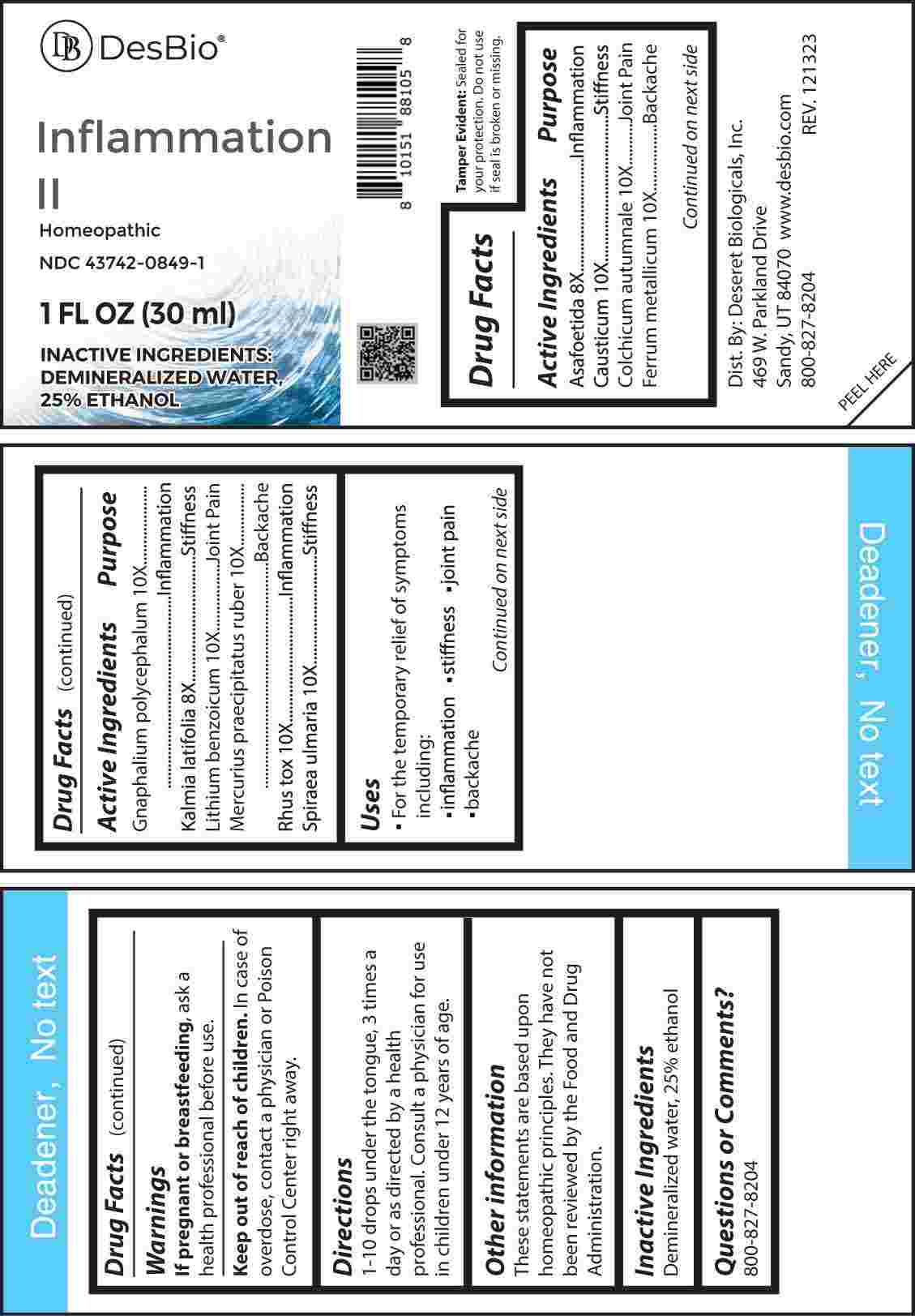 DRUG LABEL: Inflammation
NDC: 43742-0849 | Form: LIQUID
Manufacturer: Deseret Biologicals, Inc.
Category: homeopathic | Type: HUMAN OTC DRUG LABEL
Date: 20240401

ACTIVE INGREDIENTS: FERULA ASSA-FOETIDA RESIN 8 [hp_X]/1 mL; KALMIA LATIFOLIA LEAF 8 [hp_X]/1 mL; CAUSTICUM 10 [hp_X]/1 mL; COLCHICUM AUTUMNALE BULB 10 [hp_X]/1 mL; IRON 10 [hp_X]/1 mL; PSEUDOGNAPHALIUM OBTUSIFOLIUM WHOLE 10 [hp_X]/1 mL; LITHIUM BENZOATE 10 [hp_X]/1 mL; MERCURIC OXIDE 10 [hp_X]/1 mL; TOXICODENDRON PUBESCENS LEAF 10 [hp_X]/1 mL; FILIPENDULA ULMARIA ROOT 10 [hp_X]/1 mL
INACTIVE INGREDIENTS: WATER; ALCOHOL

DRUG FACTS:

ACTIVE INGREDIENTS:

Asafoetida 8X, Causticum 10X, Colchicum Autumnale 10X, Ferrum Metallicum 10X, Gnaphalium Polycephalum 10X, Kalmia Latifolia 8X, Lithium Benzoicum 10X, Mercurius Praecipitatus Ruber 10X, Rhus Tox 10X, Spiraea Ulmaria 10X.

PURPOSE:

Asafoetida - Inflammation, Causticum - Stiffness, Colchicum Autumnale – Joint Pain, Ferrum Metallicum - Backache, Gnaphalium Polycephalum - Inflammation, Kalmia Latifolia - Stiffness, Lithium Benzoicum – Joint Pain, Mercurius Praecipitatus Ruber - Backache, Rhus Tox - Inflammation, Spiraea Ulmaria - Stiffness

USES:

• For the temporary relief of the symptoms including:

• inflammation • stiffness • joint pain • backaches

These statements are based upon homeopathic principles. They have not been reviewed by the Food and Drug Administration.

WARNINGS:

If pregnant or breast-feeding, ask a health professional before use.

Keep out of reach of children. In case of overdose, contact a physician or Poison Control Center right away.

Tamper Evident: Sealed for your protection. Do not use if seal is broken or missing.

KEEP OUT OF REACH OF CHILDREN:

In case of overdose, contact a physician or Poison Control Center right away.

DIRECTIONS:

1-10 drops under the tongue, 3 times a day or as directed by a health professional. Consult a physician for use in children under 12 years of age.

INACTIVE INGREDIENTS:

Demineralized water, 25% ethanol

QUESTIONS:

Dist. By: Deseret Biologicals, Inc.
469 W. Parkland Drive
Sandy, UT 84070

www.desbio.com

800-827-8204

PACKAGE LABEL DISPLAY:

Des Bio

Inflammation II

Homeopathic

NDC 43742-0849-1

1 FL OZ (30 ml)